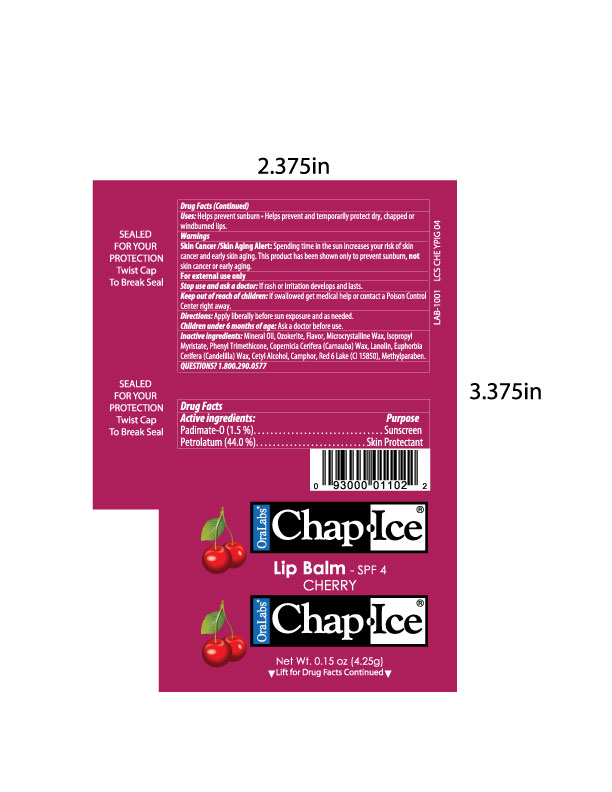 DRUG LABEL: OraLabs ChapIce Cherry SPF 4 Lip Balm
NDC: 63645-111 | Form: STICK
Manufacturer: OraLabs
Category: otc | Type: HUMAN OTC DRUG LABEL
Date: 20120911

ACTIVE INGREDIENTS: PADIMATE O 15 mg/1 g; PETROLATUM 440 mg/1 g
INACTIVE INGREDIENTS: MINERAL OIL 235 mg/1 g; CERESIN 175 mg/1 g; MICROCRYSTALLINE WAX 30 mg/1 g; PHENYL TRIMETHICONE 18.5 mg/1 g; ISOPROPYL MYRISTATE 22.3 mg/1 g; CARNAUBA WAX 10 mg/1 g; LANOLIN 10 mg/1 g; CANDELILLA WAX 5 mg/1 g; CETYL ALCOHOL 5 mg/1 g; CAMPHOR (SYNTHETIC) 2 mg/1 g; METHYLPARABEN 1 mg/1 g; CHERRY 30 mg/1 g; D&C RED NO. 6 12 mg/1 g

Drug Facts

Active ingredient

Padimate O

Petrolatum

Purpose

Sunscreen

Skin Protectant

Uses

Helps prevent sunscreen

Warnings

Skin Cancer/Skin Aging Alert: Spending time in the sun increases your risk of skin cancer and early skin aging. This product has been shown only to prevent sunburn, not skin cancer or early aging.

For external use only

Stop use and ask a doctor: if rash or irritation develops and lasts.

Keep out of reach of children: if swallowed get medical help or contact a Poison Control Center right away.

Directions

Apply liberally before sun exposure and as needed.

Children under the age of 6 months: Ask a doctor before use.

Inactive ingredients

Mineral oil, Ozokerite, Flavor, Microcrystalline Wax, Isopropyl Myristate, Phenyl Trimethicone, Copernicia Cerifera (Carnauba) Wax, Lanolin, Euphorbia Cerifera (Candellia) Wax, Cetyl Alcohol, Campor, Red 6 Lake (C15850), Methylparaben